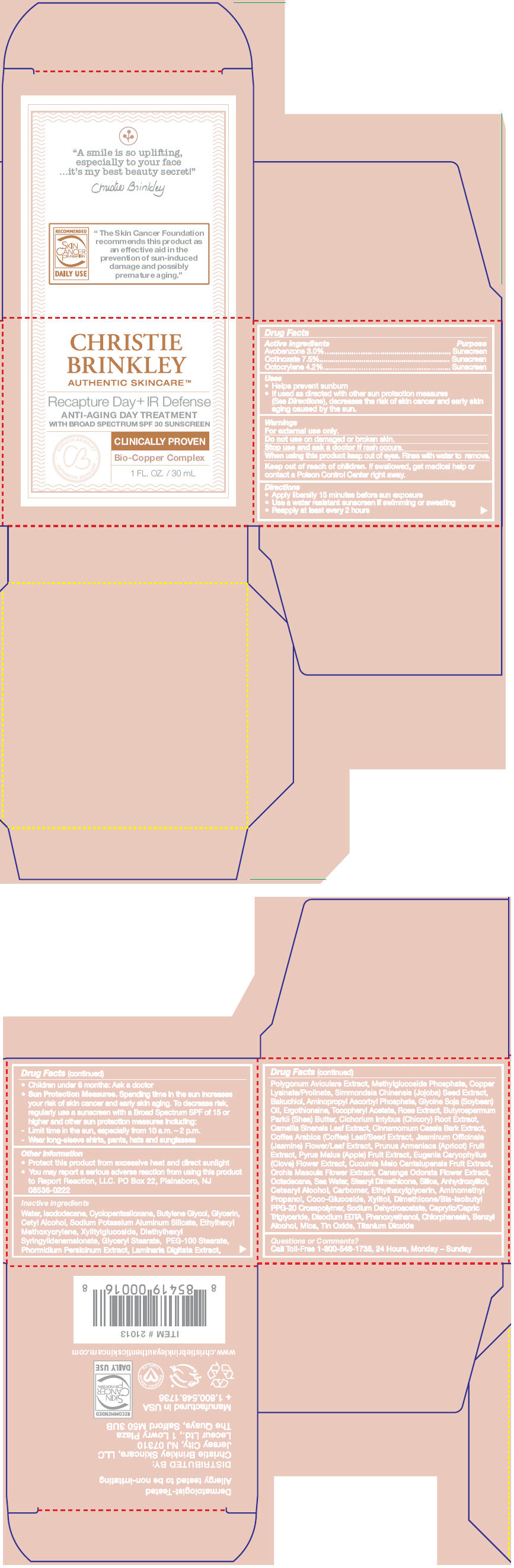 DRUG LABEL: Recapture Day Plus IR Defense
NDC: 70550-000 | Form: CREAM
Manufacturer: Atlantic Coast Media Group, LLC.
Category: otc | Type: HUMAN OTC DRUG LABEL
Date: 20170124

ACTIVE INGREDIENTS: AVOBENZONE 30 mg/1 mL; OCTOCRYLENE 42 mg/1 mL; OCTINOXATE 75 mg/1 mL
INACTIVE INGREDIENTS: ISODODECANE; CYCLOMETHICONE 5; BUTYLENE GLYCOL; GLYCERIN; CETYL ALCOHOL; ETHYLHEXYL METHOXYCRYLENE; XYLITYLGLUCOSIDE; DIETHYLHEXYL SYRINGYLIDENEMALONATE; GLYCERYL MONOSTEARATE; PEG-100 STEARATE; PHORMIDIUM PERSICINUM; LAMINARIA DIGITATA; POLYGONUM AVICULARE TOP; SIMMONDSIA CHINENSIS SEED; BAKUCHIOL; AMINOPROPYL ASCORBYL PHOSPHATE; SOYBEAN OIL; ERGOTHIONEINE; .ALPHA.-TOCOPHEROL ACETATE; SHEA BUTTER; CHICORY ROOT; GREEN TEA LEAF; CHINESE CINNAMON; JASMINUM OFFICINALE FLOWER; APRICOT; APPLE; CLOVE; CANTALOUPE; ORCHIS MASCULA FLOWER; CANANGA ODORATA FLOWER; OCTADECANE; SODIUM CHLORIDE; STEARYL DIMETHICONE (400 MPA.S AT 50C); SILICON DIOXIDE; ANHYDROXYLITOL; CETOSTEARYL ALCOHOL; CARBOXYPOLYMETHYLENE; ETHYLHEXYLGLYCERIN; AMINOMETHYLPROPANOL; COCO GLUCOSIDE; XYLITOL; DIMETHICONE/BIS-ISOBUTYL PPG-20 CROSSPOLYMER; SODIUM DEHYDROACETATE; MEDIUM-CHAIN TRIGLYCERIDES; EDETATE DISODIUM; PHENOXYETHANOL; CHLORPHENESIN; BENZYL ALCOHOL; MICA; STANNIC OXIDE; TITANIUM DIOXIDE

Recapture Day + IR Defense

Drug Facts

ACTIVE INGREDIENT

Active ingredients | Purpose
Avobenzone 3.0% | Sunscreen
Octinoxate 7.5% | Sunscreen
Octocrylene 4.2% | Sunscreen

Uses

- Helps prevent sunburn
- If used as directed with other sun protection measures (See Directions), decreases the risk of skin cancer and early skin aging caused by the sun.

Warnings

For external use only.

Do not use on damaged or broken skin.

Stop use and ask a doctor if rash occurs.

When using this product keep out of eyes. Rinse with water to remove.

Keep out of reach of children. If swallowed, get medical help or contact a Poison Control Center right away.

Directions

- Apply liberally 15 minutes before sun exposure
- Use a water resistant sunscreen if swimming or sweating
- Reapply at least every 2 hours
- Children under 6 months: Ask a doctor
- Sun Protection Measures. Spending time in the sun increases your risk of skin cancer and early skin aging. To decrease risk, regularly use a sunscreen with a Broad Spectrum SPF of 15 or higher and other sun protection measures including:
  - Limit time in the sun, especially from 10 a.m. – 2 p.m.
  - Wear long-sleeve shirts, pants, hats and sunglasses

Other information

- Protect this product from excessive heat and direct sunlight
- You may report a serious adverse reaction from using this product to Report Reaction, LLC. PO Box 22, Plainsboro, NJ 08536-0222

Inactive ingredients

Water, Isododecane, Cyclopentasiloxane, Butylene Glycol, Glycerin, Cetyl Alcohol, Sodium Potassium Aluminum Silicate, Ethylhexyl Methoxycrylene, Xylitylglucoside, Diethylhexyl Syringylidenemalonate, Glyceryl Stearate, PEG-100 Stearate, Phormidium Persicinum Extract, Laminaria Digitata Extract, Polygonum Aviculare Extract, Methylglucoside Phosphate, Copper Lysinate/Prolinate, Simmondsia Chinensis (Jojoba) Seed Extract, Bakuchiol, Aminopropyl Ascorbyl Phosphate, Glycine Soja (Soybean) Oil, Ergothioneine, Tocopheryl Acetate, Rose Extract, Butyrospermum Parkii (Shea) Butter, Cichorium Intybus (Chicory) Root Extract, Camellia Sinensis Leaf Extract, Cinnamomum Cassia Bark Extract, Coffea Arabica (Coffee) Leaf/Seed Extract, Jasminum Officinale (Jasmine) Flower/Leaf Extract, Prunus Armeniaca (Apricot) Fruit Extract, Pyrus Malus (Apple) Fruit Extract, Eugenia Caryophyllus (Clove) Flower Extract, Cucumis Melo Cantalupensis Fruit Extract, Orchis Mascula Flower Extract, Cananga Odorata Flower Extract, Octadecane, Sea Water, Stearyl Dimethicone, Silica, Anhydroxylitol, Cetearyl Alcohol, Carbomer, Ethylhexylglycerin, Aminomethyl Propanol, Coco-Glucoside, Xylitol, Dimethicone/Bis-Isobutyl PPG-20 Crosspolymer, Sodium Dehydroacetate, Caprylic/Capric Triglyceride, Disodium EDTA, Phenoxyethanol, Chlorphenesin, Benzyl Alcohol, Mica, Tin Oxide, Titanium Dioxide

Questions or Comments?

Call Toll-Free 1-800-548-1736, 24 Hours, Monday – Sunday

DISTRIBUTED BY:
Christie Brinkley Skincare, LLC
Jersey City, NJ 07310

PRINCIPAL DISPLAY PANEL - 30 mL Jar Carton

CHRISTIE
BRINKLEY
AUTHENTIC SKINCARE™

Recapture Day + IR Defense
ANTI-AGING DAY TREATMENT
WITH BROAD SPECTRUM SPF 30 SUNSCREEN

• CHRISTIE BRINKLEY •
AUTHENTIC SKINCARE

CLINICALLY PROVEN
Bio-Copper Complex

1 FL. OZ. / 30 mL